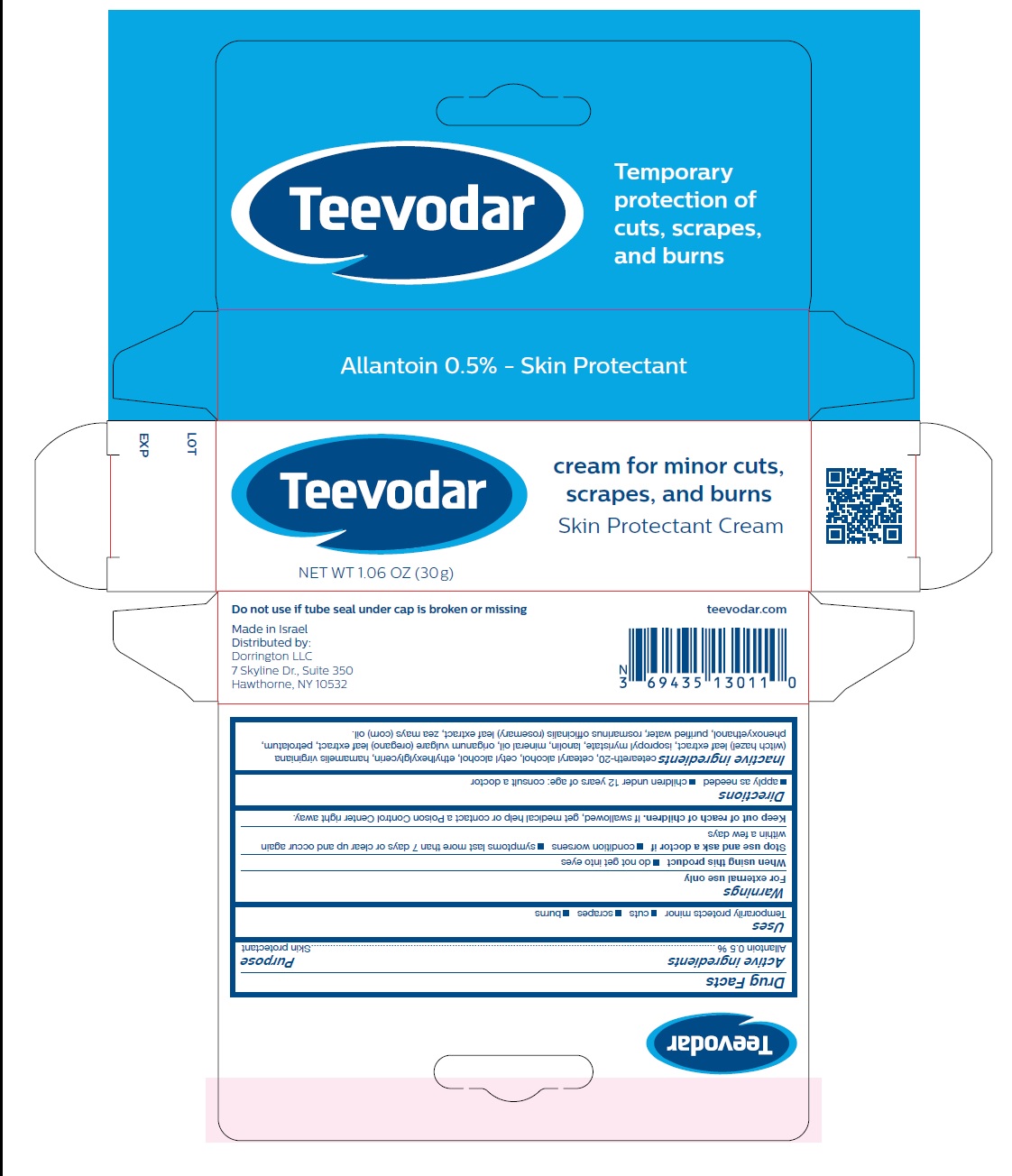 DRUG LABEL: Teevodar
NDC: 69435-1301 | Form: CREAM
Manufacturer: PEER PHARM LTD.
Category: otc | Type: HUMAN OTC DRUG LABEL
Date: 20260112

ACTIVE INGREDIENTS: ALLANTOIN 0.5 g/100 g
INACTIVE INGREDIENTS: POLYOXYL 20 CETOSTEARYL ETHER; CETOSTEARYL ALCOHOL; CETYL ALCOHOL; ETHYLHEXYLGLYCERIN; HAMAMELIS VIRGINIANA LEAF; ISOPROPYL MYRISTATE; LANOLIN; MINERAL OIL; OREGANO; PETROLATUM; PHENOXYETHANOL; WATER; ROSEMARY; CORN OIL

Teevodar 30g

Active Ingredient

Allantoin 0.5%

Purpose

Skin Protectant

Uses

Temporarily protects minor cuts scrapes burns

Warnings

- For external use only
- When using this productdo not get into eyes
- Stop use and ask a doctor if
- contition worsens
- symptoms last more than 7 days or clear up and occur again within a few days
- Keep out of reach of children.If swallowed, get medical help or contact a Poison Control Center right away.

Directions

- Apply as needed.
- Children under 12 years of age: consult a doctor

Inactive Ingredients

Ceteareth-20, Cetearyl alcohol, Cetyl alcohol, ethylhexylglycerin, Hamamelis virginiana (witch hazel) leaf extract, Isopropyl myristate, Lanolin, Mineral oil, Origanum vulgare (oregano) leaf extract, Petrolatum, Phenoxyethanol, Purified water, Rosmarinus officinalis (rosemary) leaf extract, Zea mayes (corn) oil